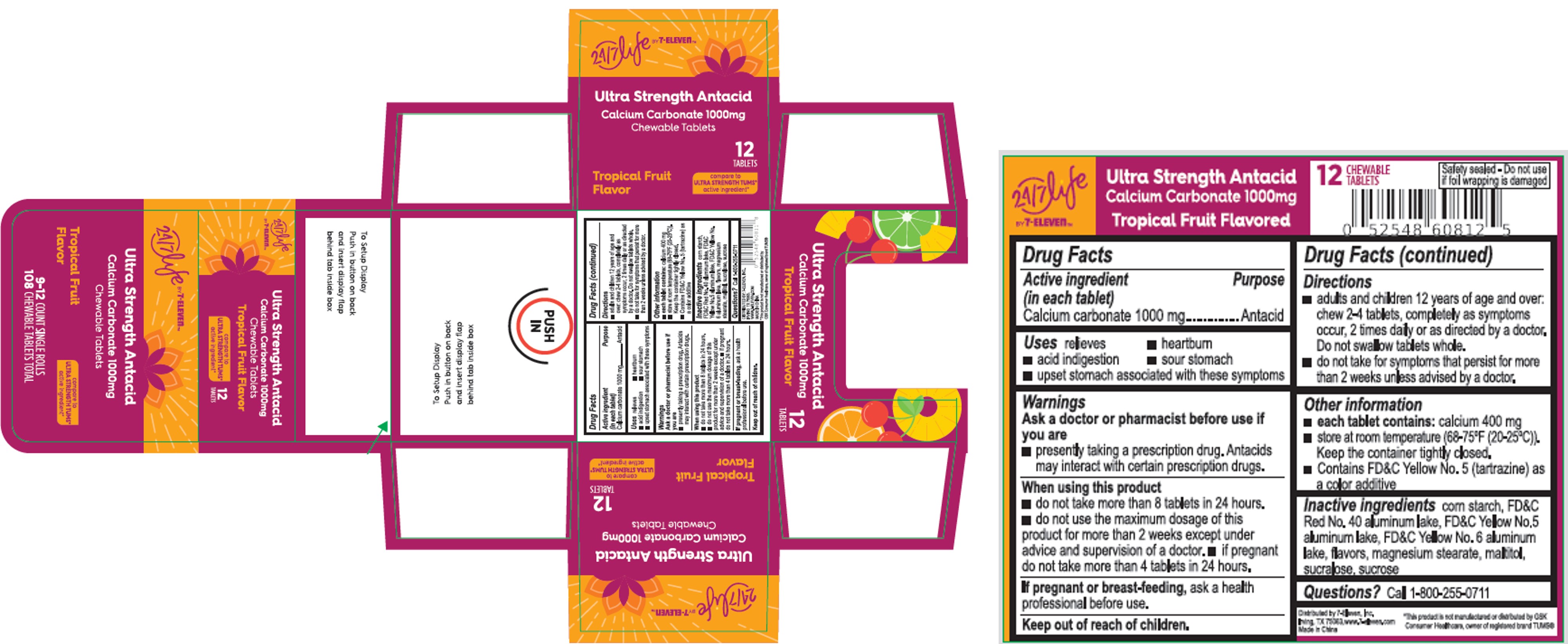 DRUG LABEL: Ultra Strength Antacid Tropical Fruit Flavor
NDC: 10202-011 | Form: TABLET, CHEWABLE
Manufacturer: 7-ELEVEN
Category: otc | Type: HUMAN OTC DRUG LABEL
Date: 20251219

ACTIVE INGREDIENTS: CALCIUM CARBONATE 1000 mg/1 1
INACTIVE INGREDIENTS: STARCH, CORN; FD&C RED NO. 40 ALUMINUM LAKE; SUCRALOSE; MALTITOL; SUCROSE; MAGNESIUM STEARATE; FD&C YELLOW NO. 5 ALUMINUM LAKE; FD&C YELLOW NO. 6 ALUMINUM LAKE

7-Eleven Xiamen MGC Tropical Fruit

Active ingredient (in each tablet)

Calcium carbonate 1000 mg

Purpose

Antacid

Uses

Relieves

- heartburn
- acid indigestion
- sour stomach
- upset stomach associated with these symptoms

Warnings

Ask a doctor or pharmacist before use if you are

- presently taking a prescription drug. Antacids may interact with certain perscription drugs.

When using this product

- do not take more than 8 tablets in 24 hours
- do not use the maximum dosage of this product for more than 2 weeks except under the advice and supervision of a doctor
- if pregnant do not take more than 4 tablets in 24 hours

PREGNANCY OR BREAST FEEDING

If pregnant or breast-feeding, ask a health professional before use

Keep out of reach of children.

Directions

- Adults and children 12 years of age and over: chew 2-3 tablets, completely as symptoms occur, 2 times daily or as directed by a doctor. Do not swallow tablets whole.
- Do not take for symptoms that persist for mare than 2 weeks unless advised by a doctor

Other Information

- each tablet contains: calcium 400 mg
- store at room temperature (68-75ºF (20-25ºC)). Keep container tightly closed.
- Contains FD&C Yellow No. 5 (tartrazine) as a color additive.

Inactive ingredients

corn starch, FD&C Red No.40 aluminum lake, FD&C Yellow No.5 aluminum lake, FD&C Yellow No.6 aluminum lake, flavor, magnesium stearate, maltitol, sucralose, sucrose

Questions?Call 1-800-255-0711